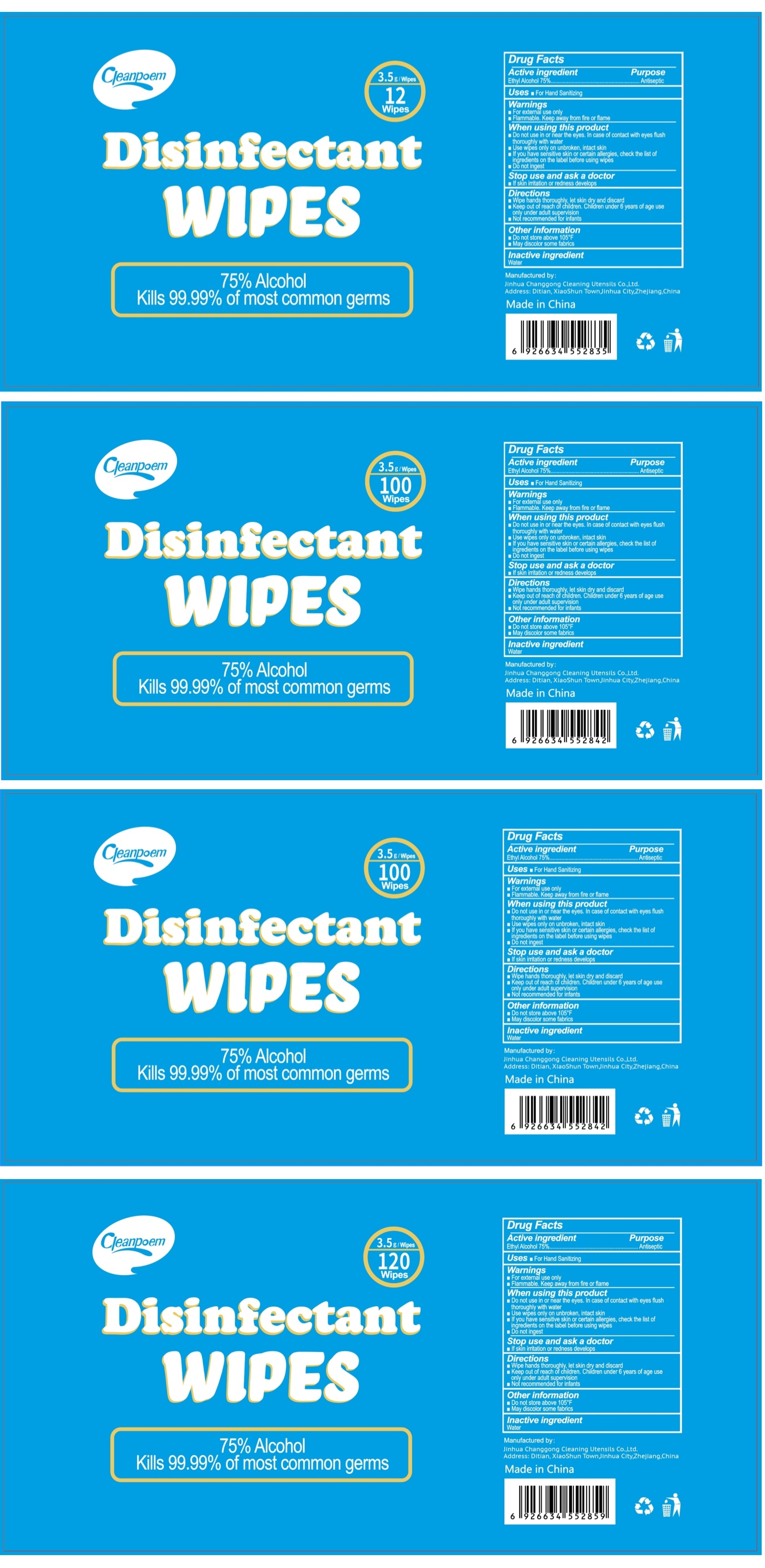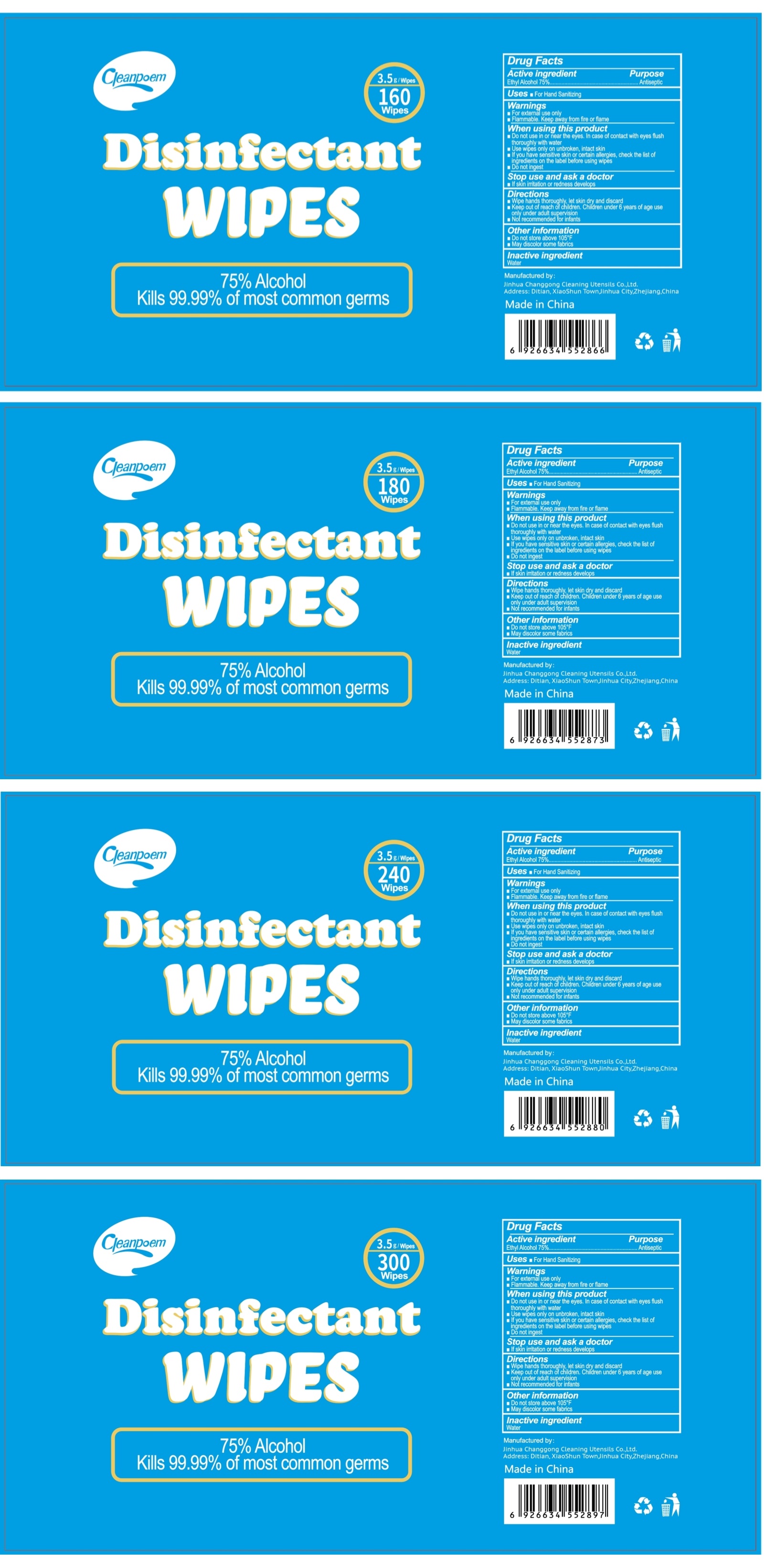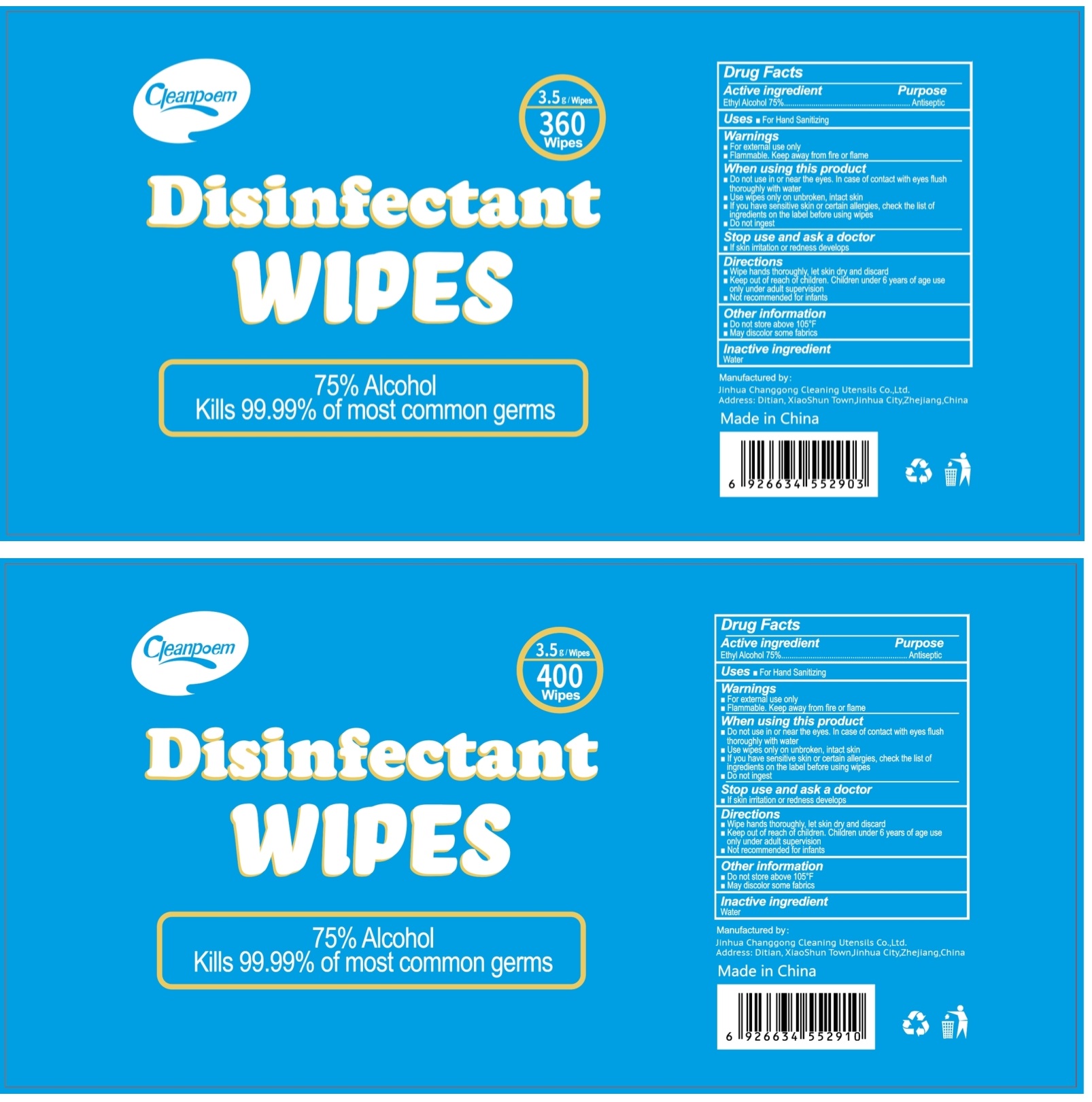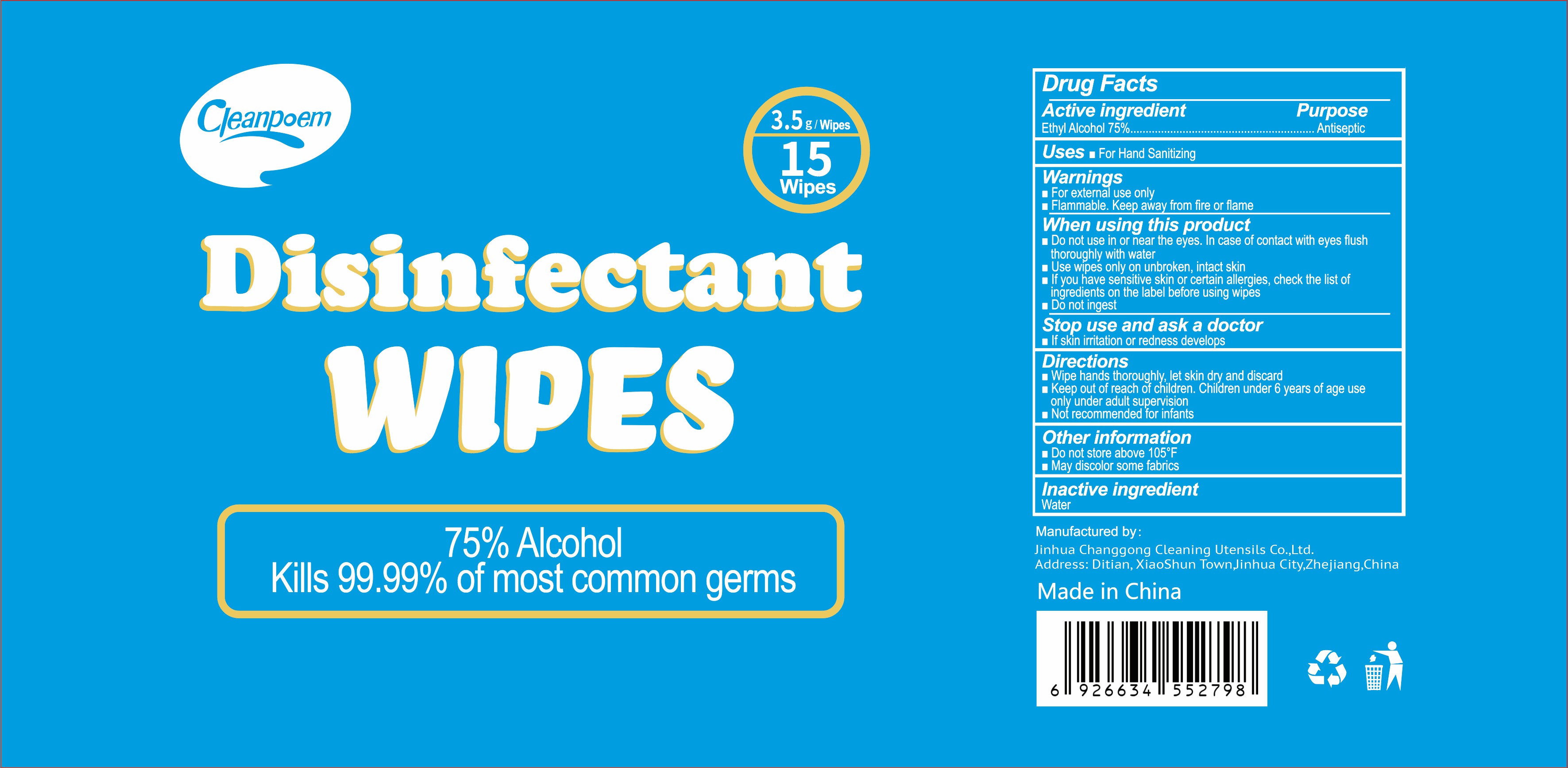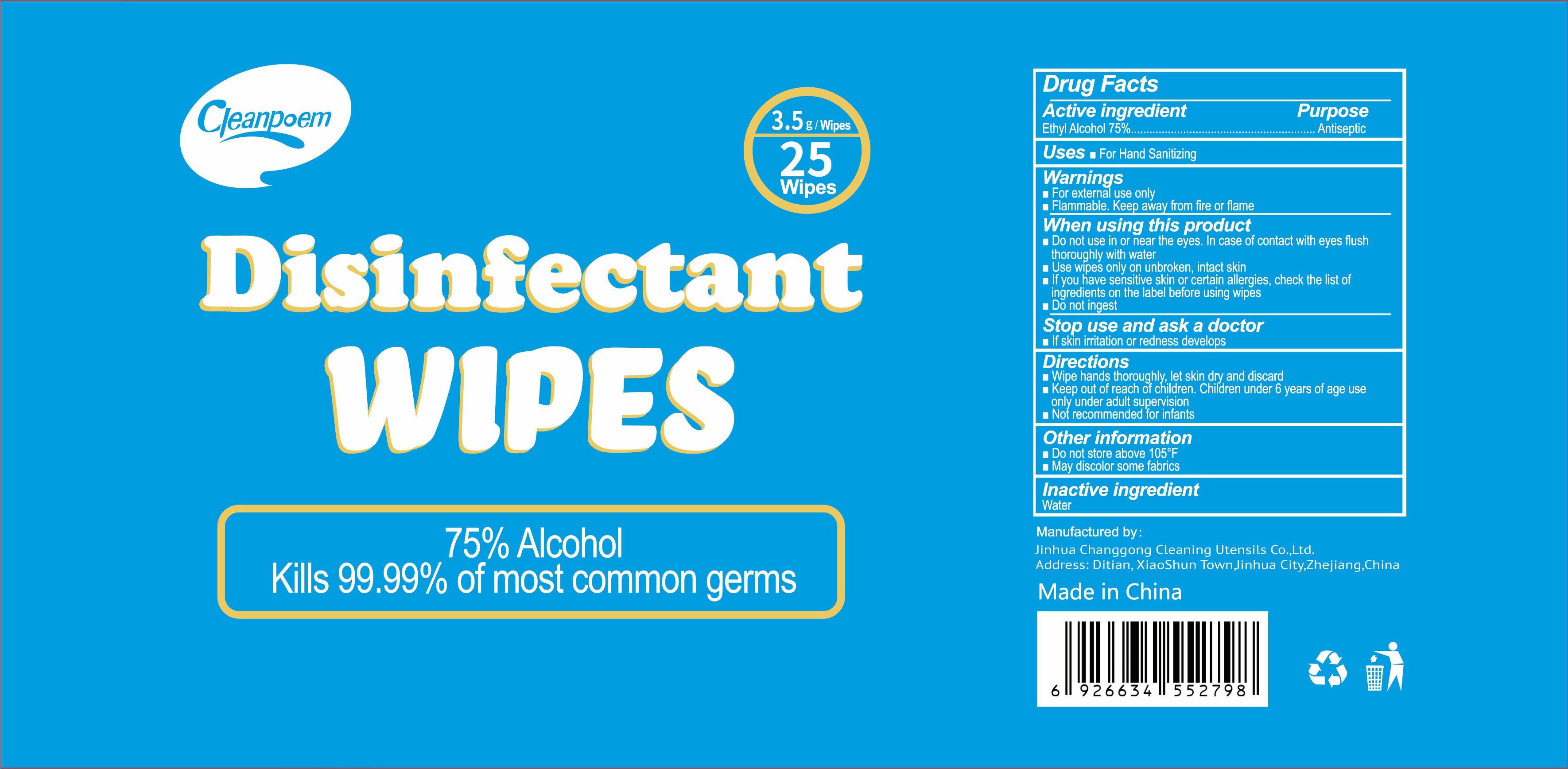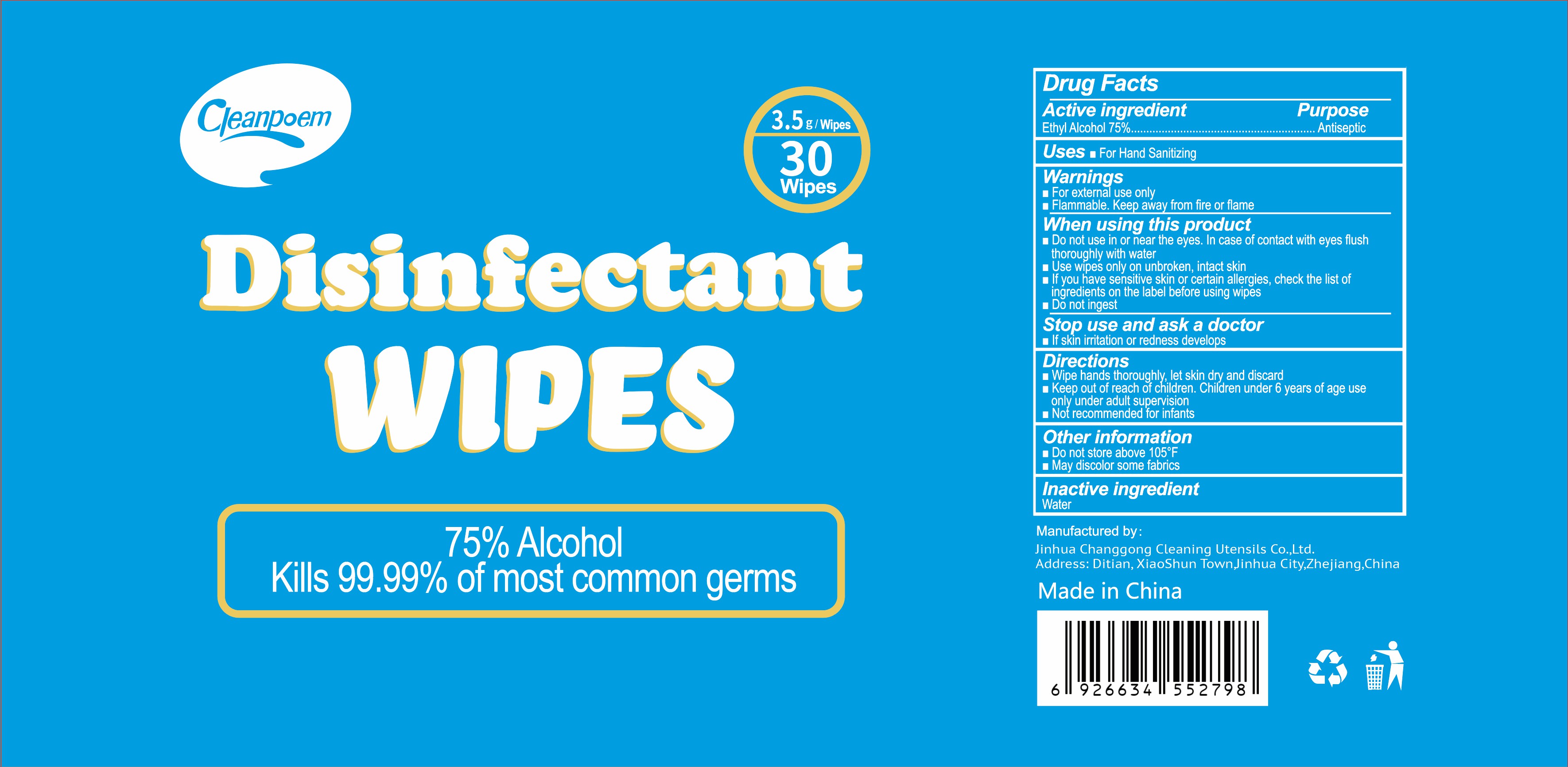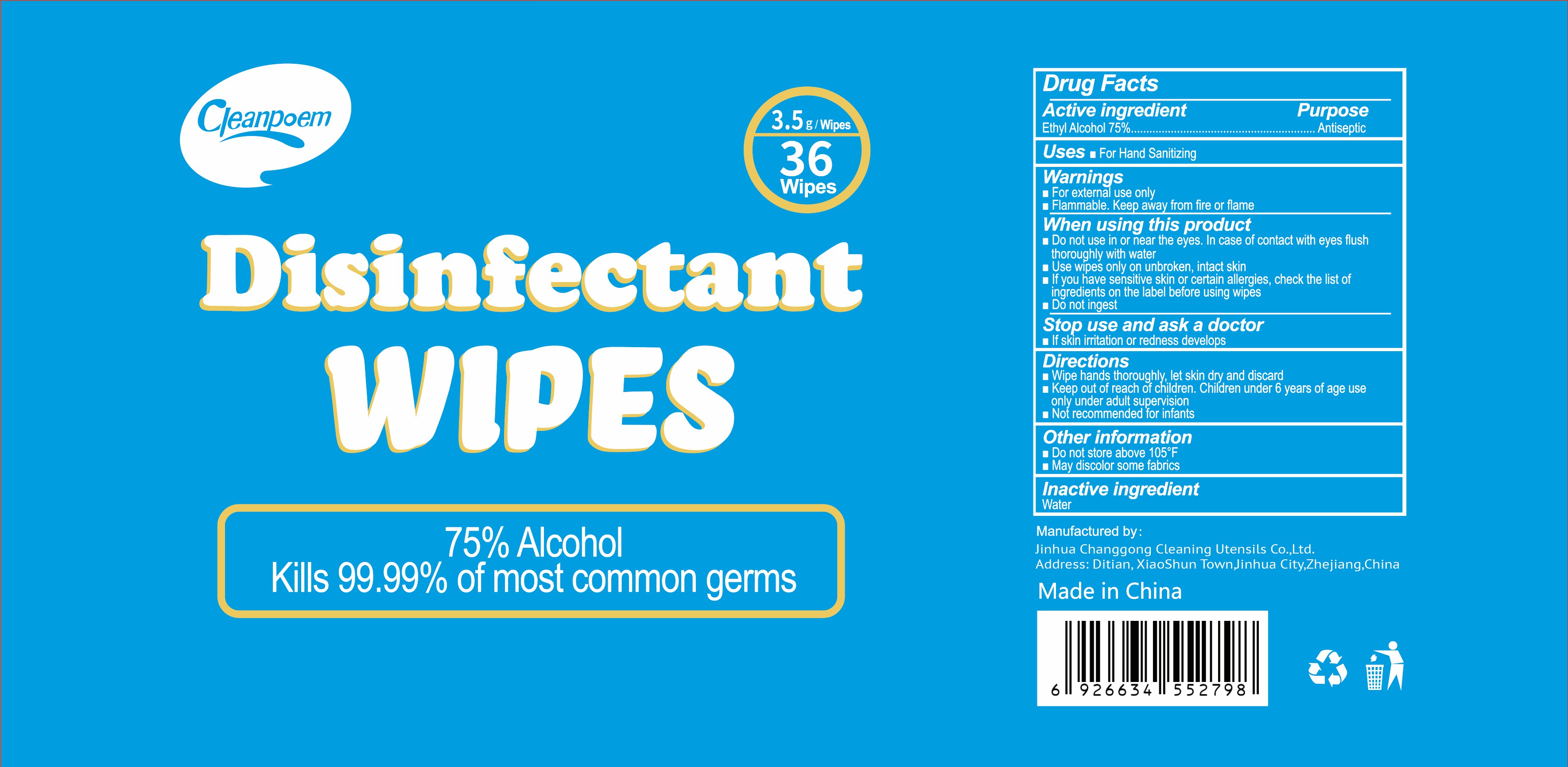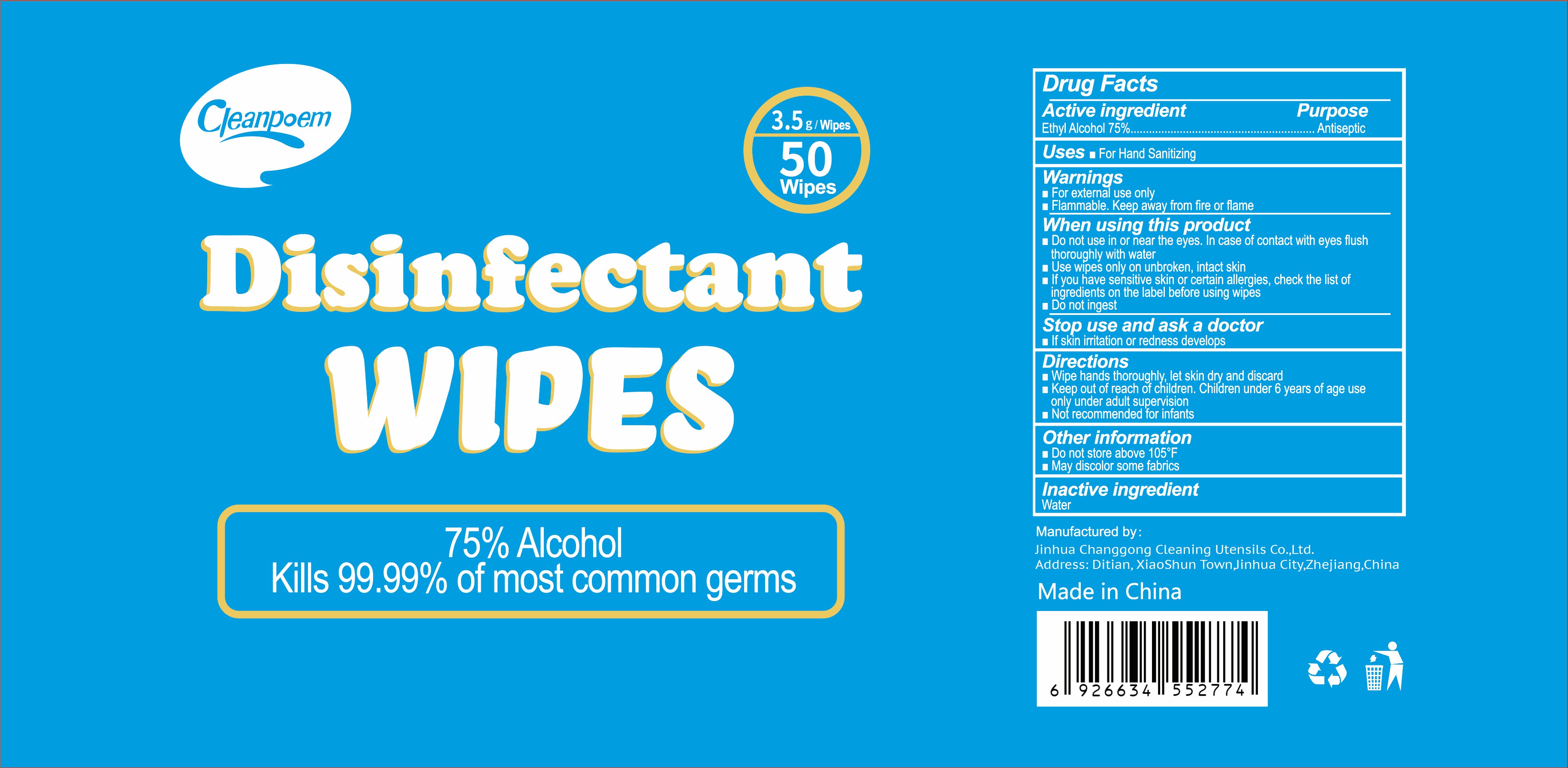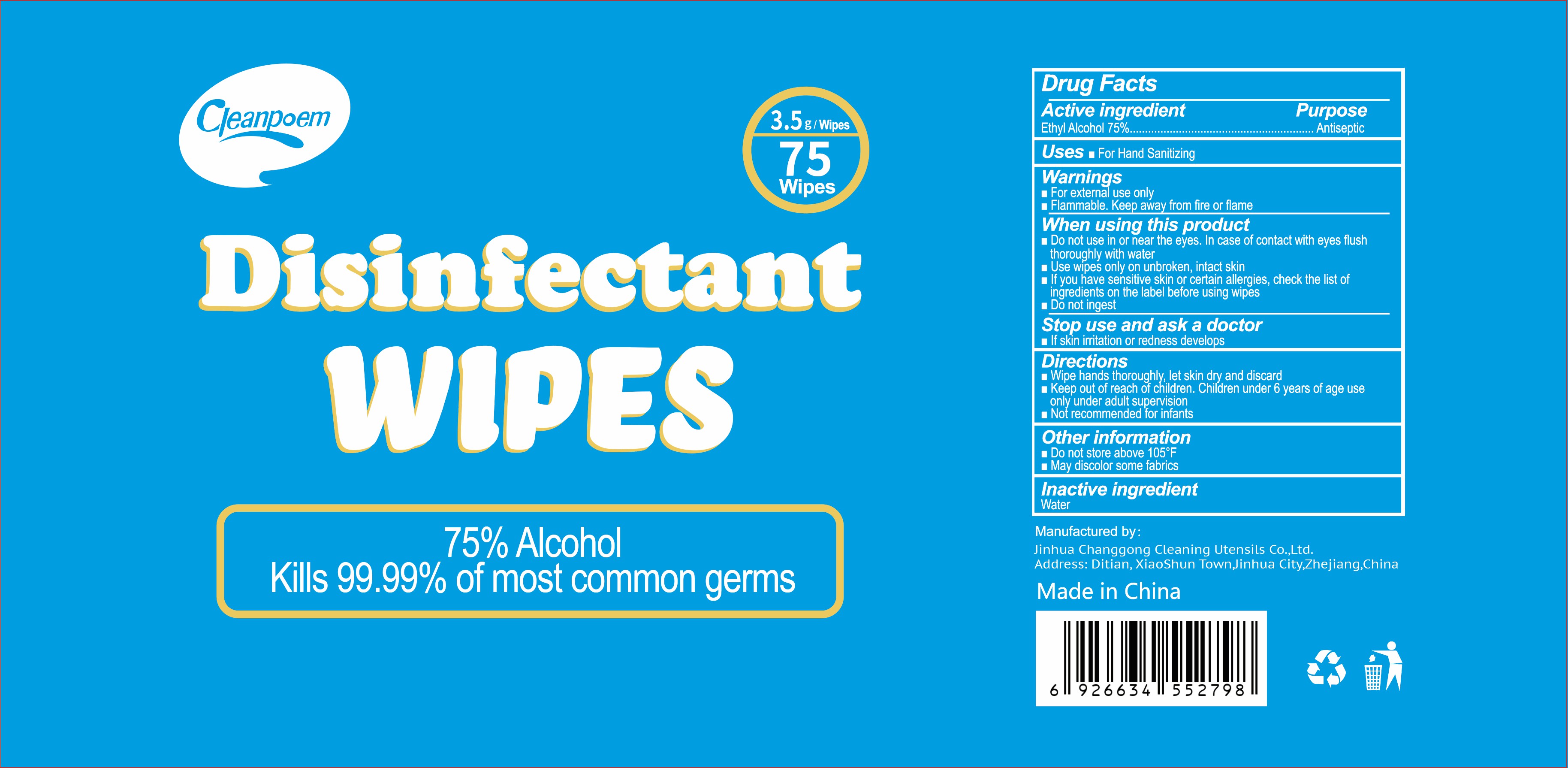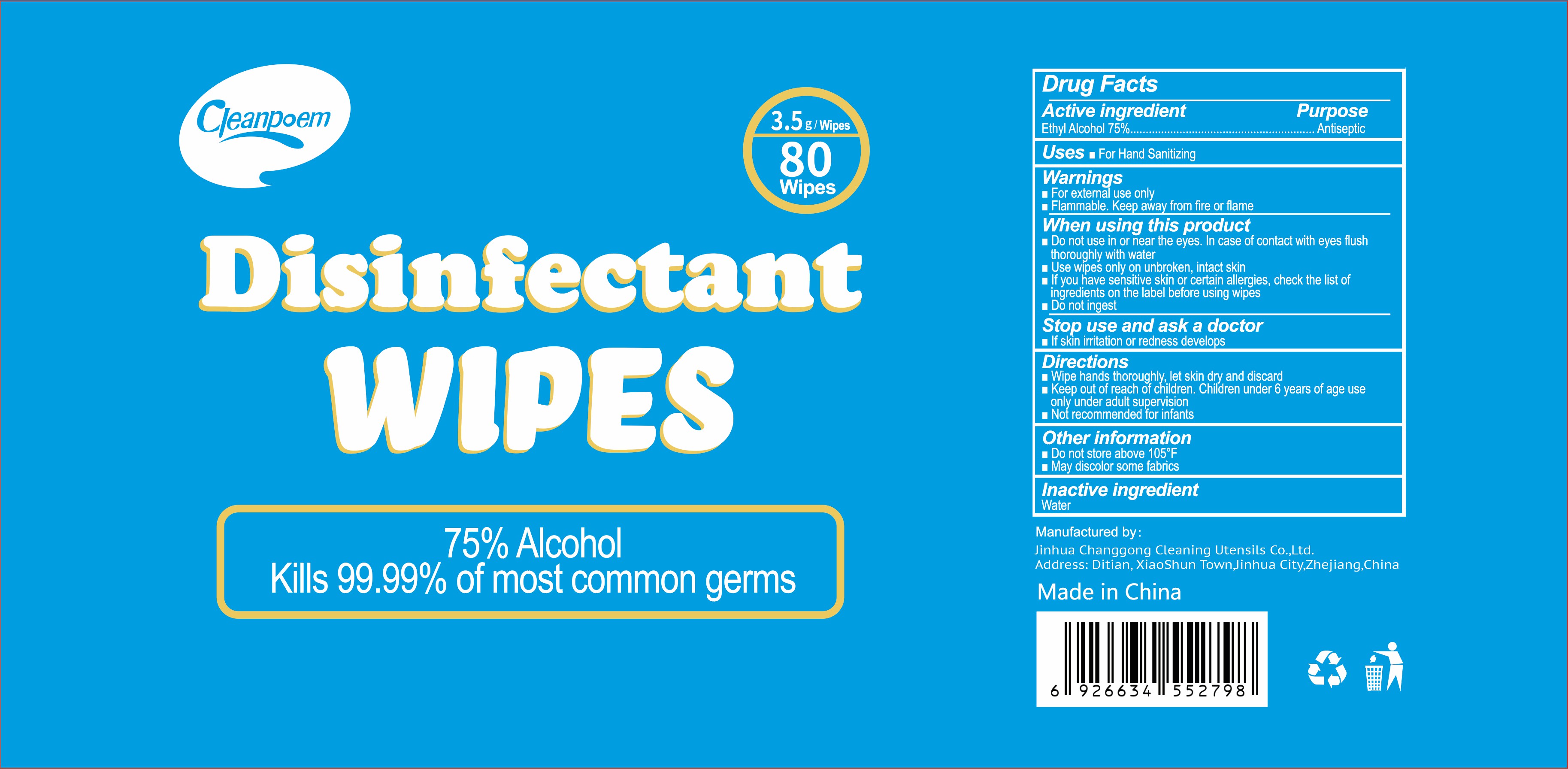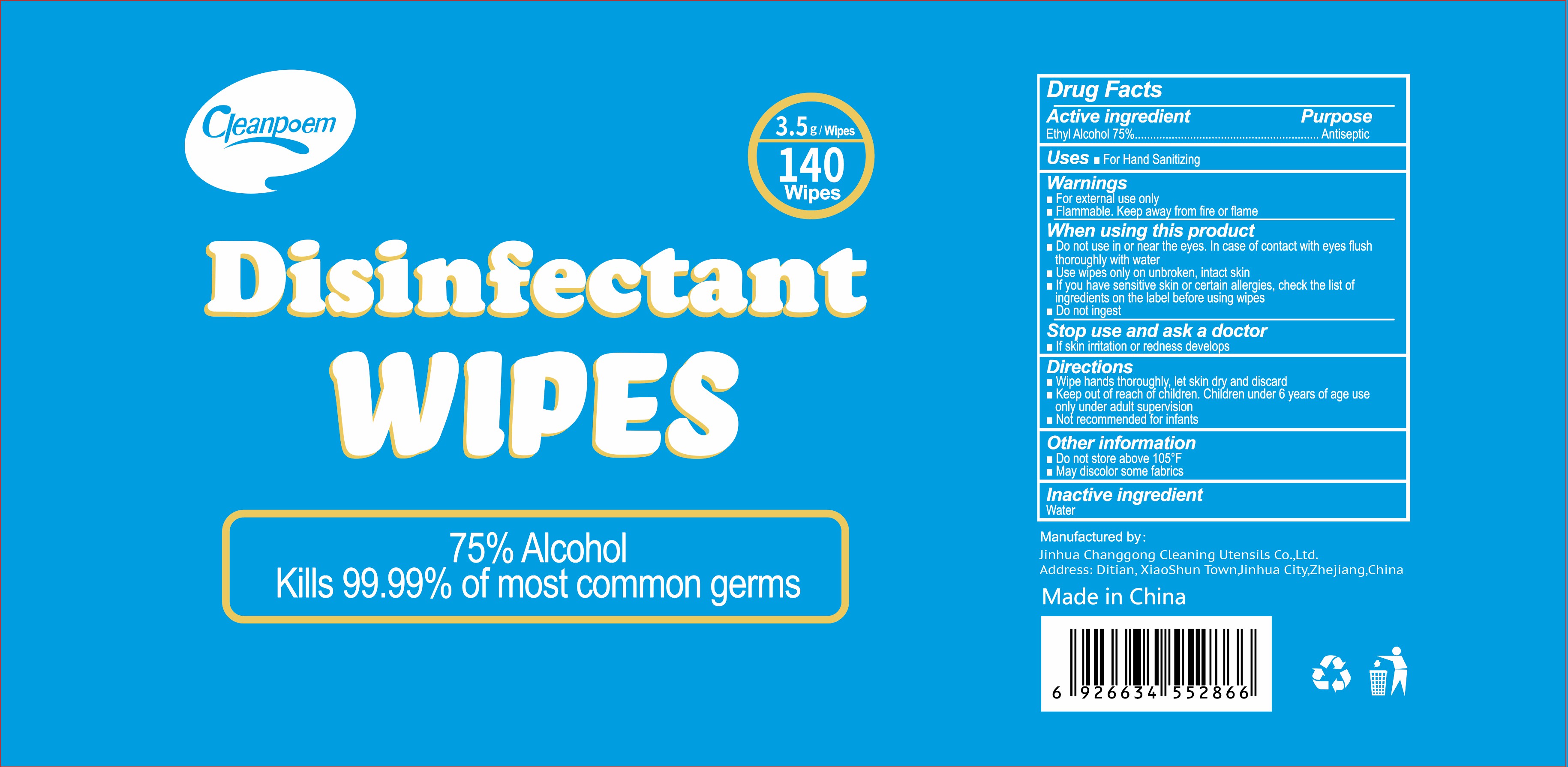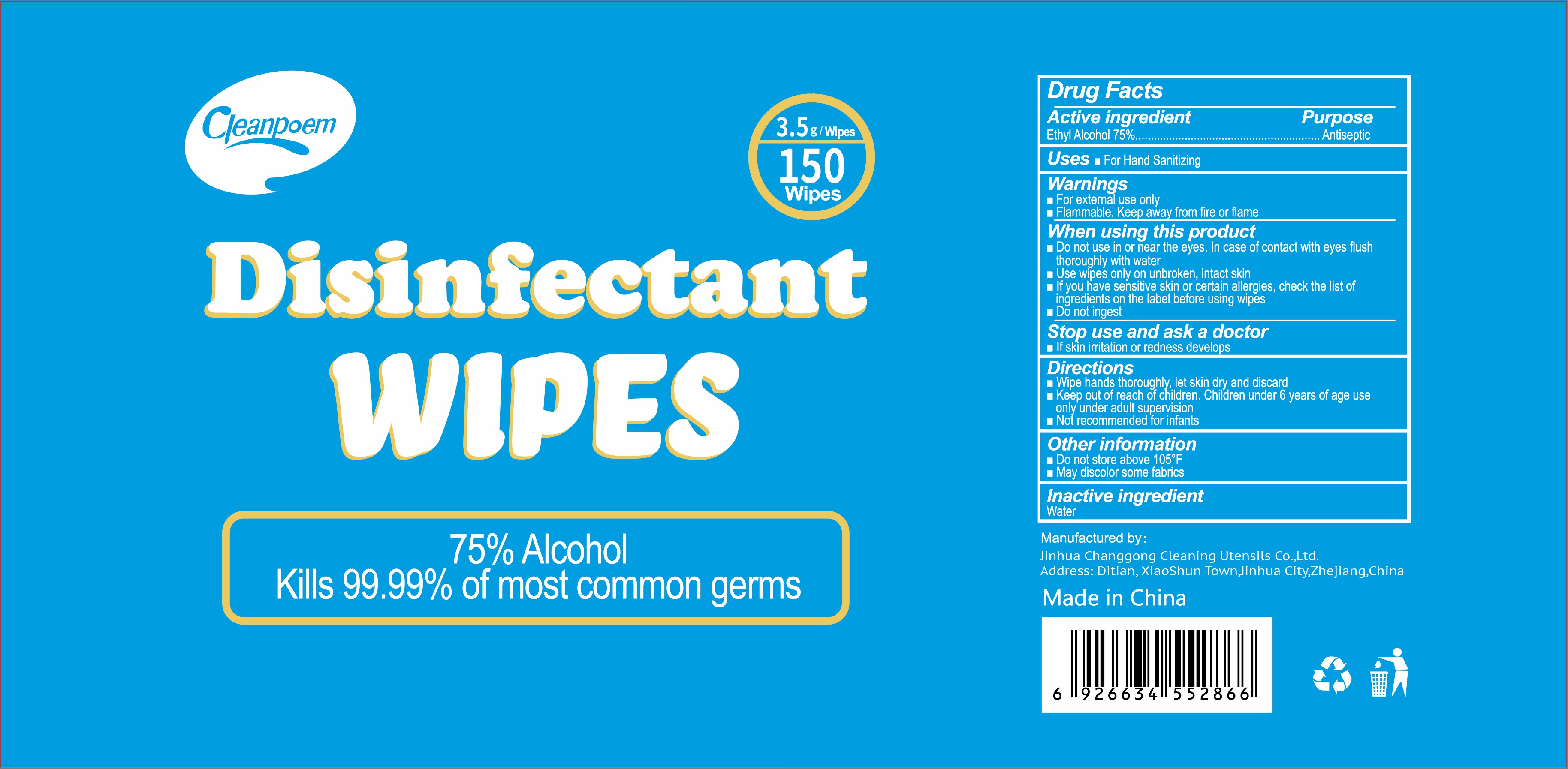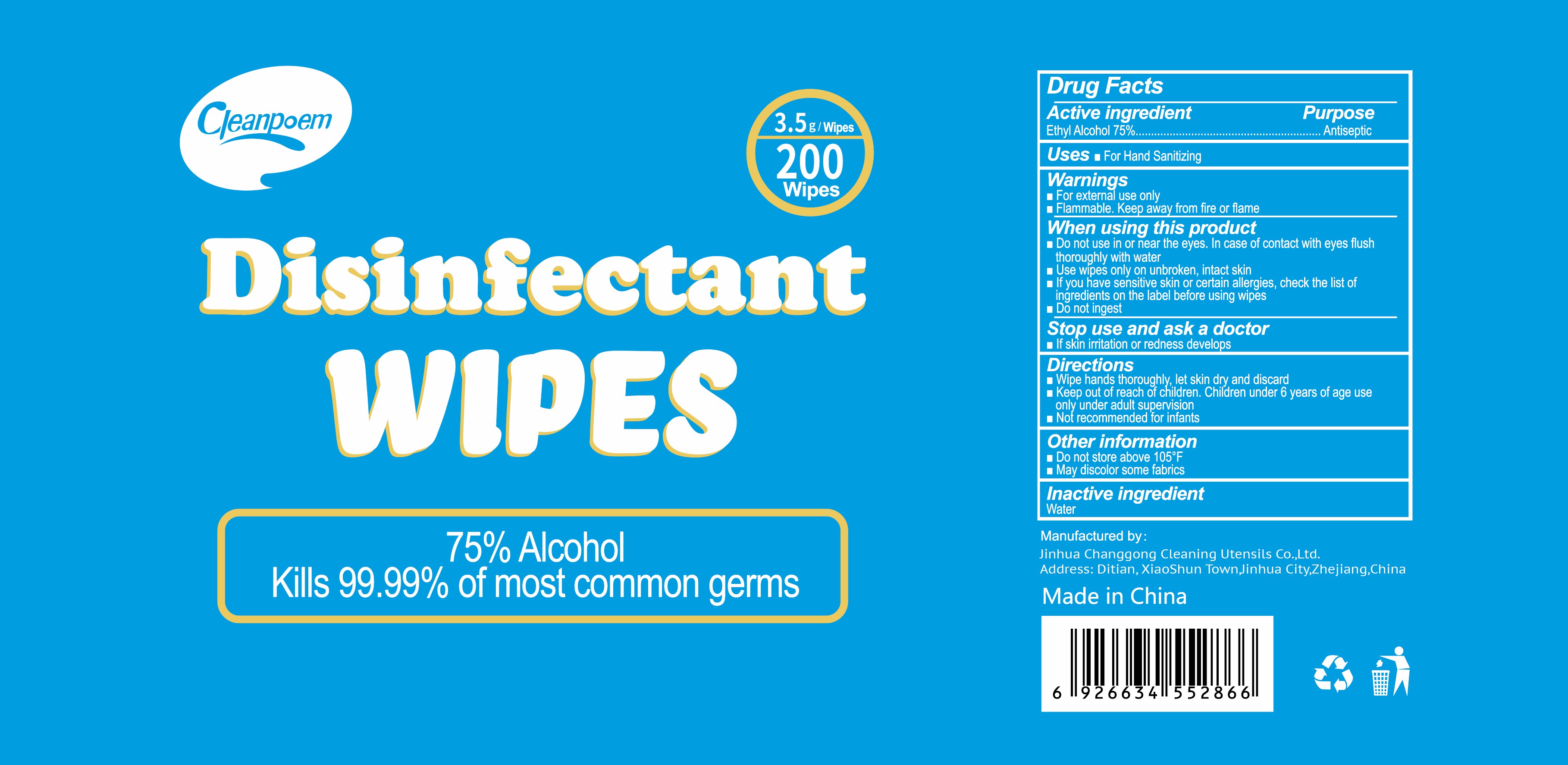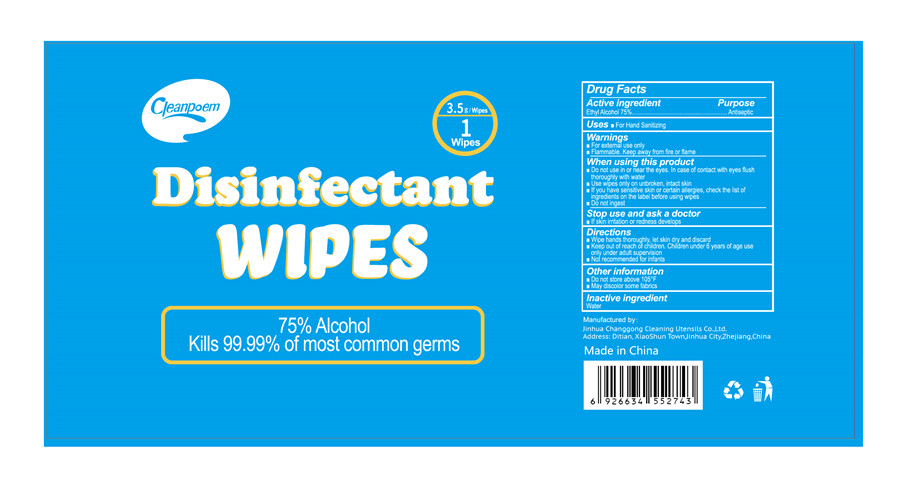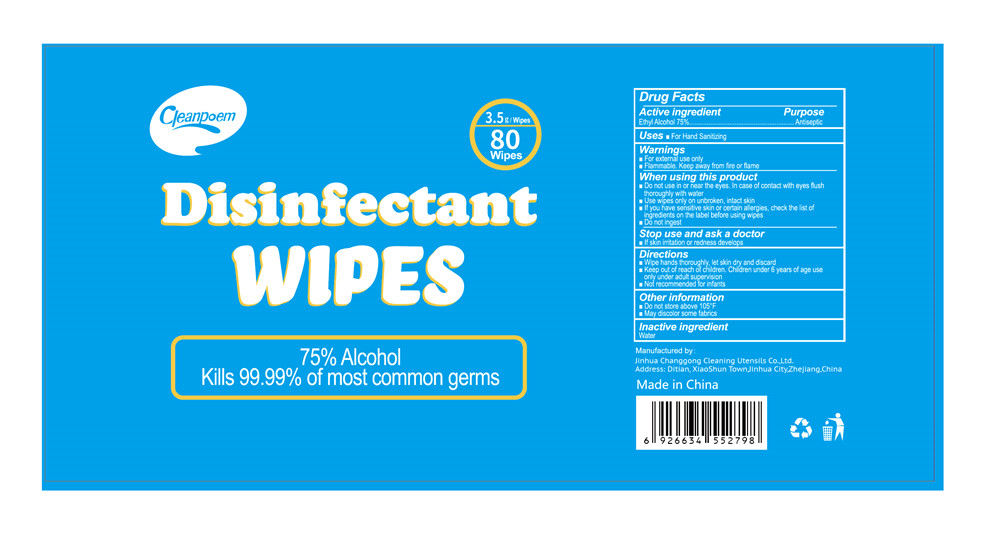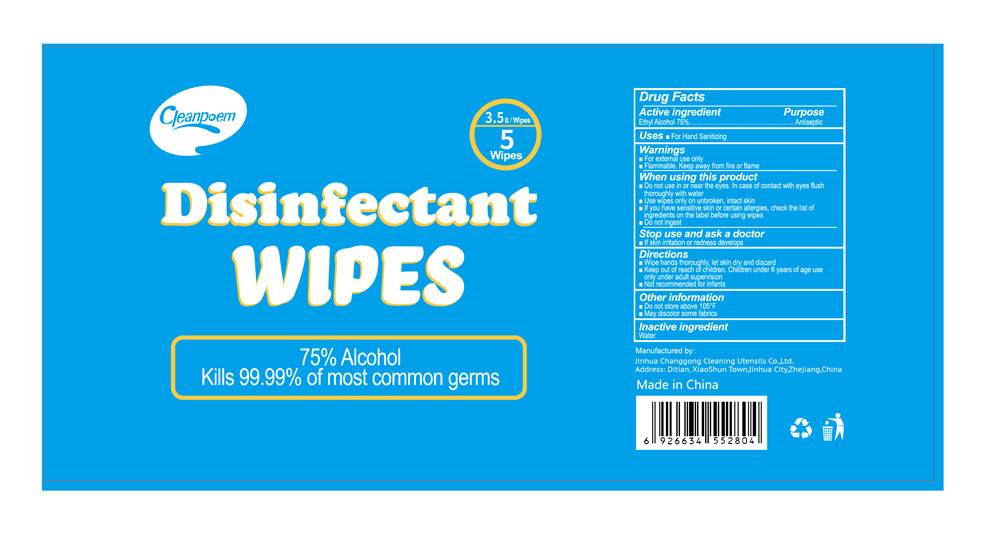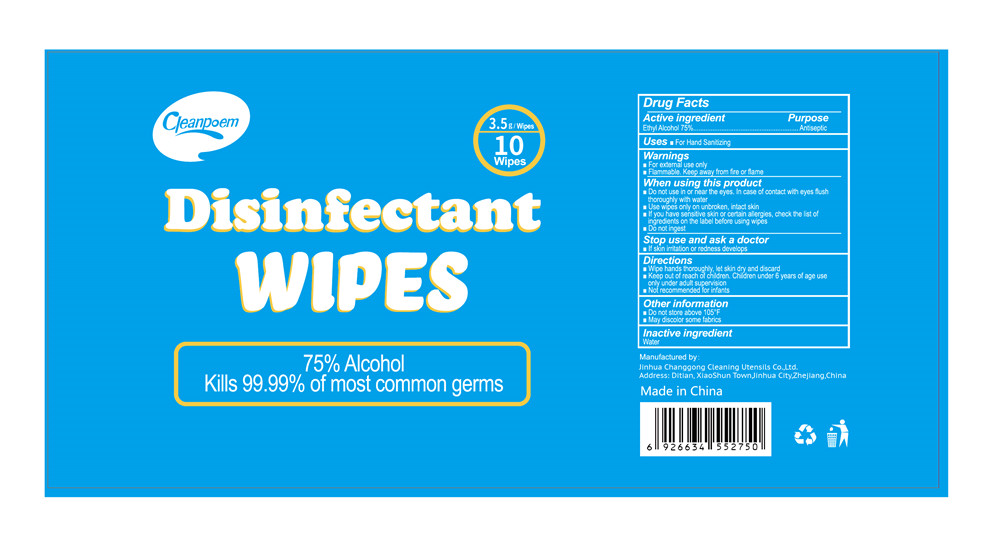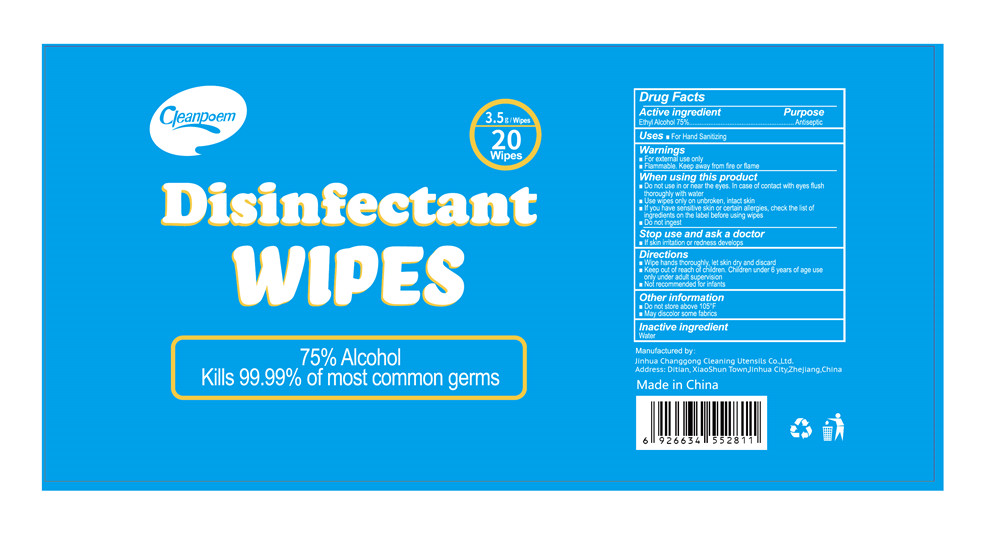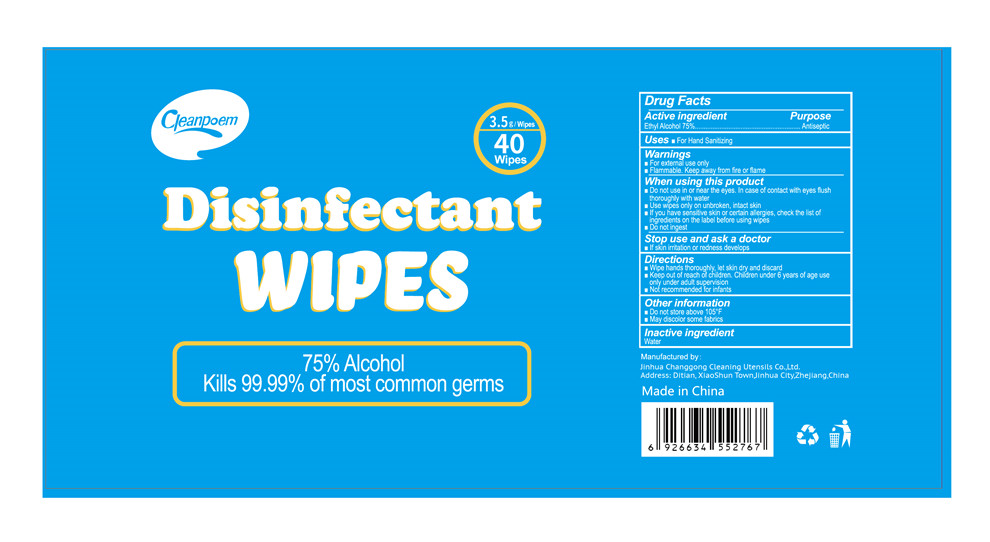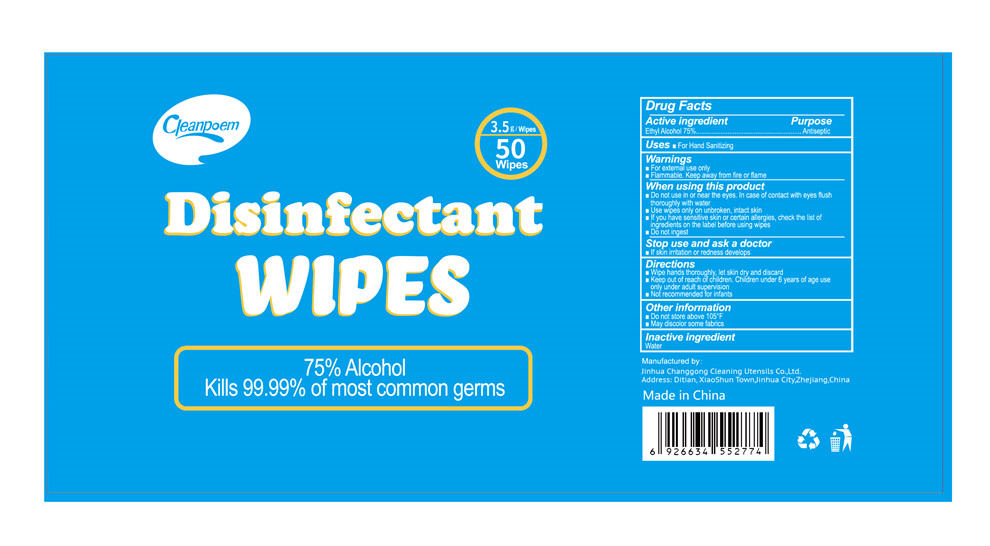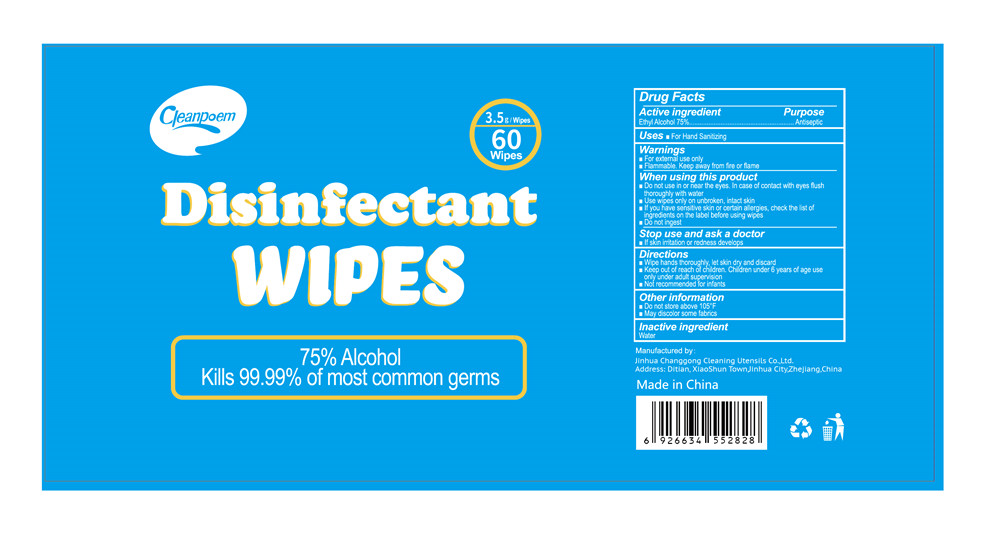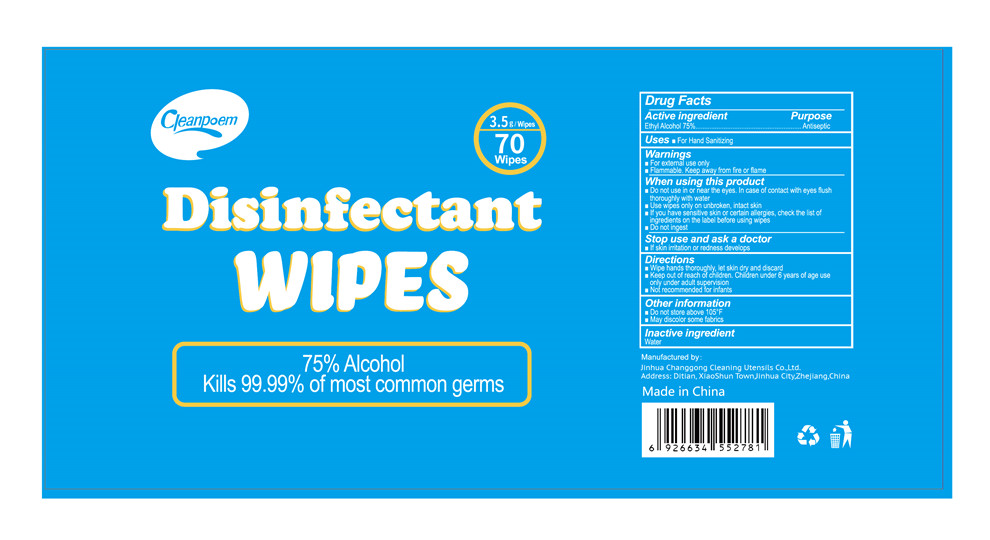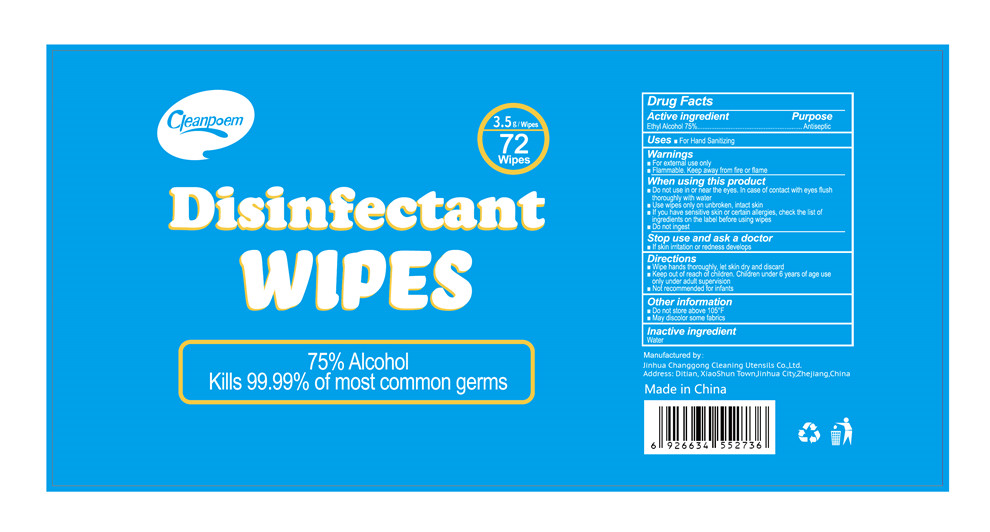 DRUG LABEL: disinfectant wipes
NDC: 78505-002 | Form: CLOTH
Manufacturer: JINHUA CHANG GONG CLEANING UTENSILS CO.,LTD
Category: otc | Type: HUMAN OTC DRUG LABEL
Date: 20210329

ACTIVE INGREDIENTS: ALCOHOL 75 g/100 g
INACTIVE INGREDIENTS: WATER

78505-002
disinfectant wipes

Active ingredient

Ethyl Alcohol 75%

Purpose

Antiseptic

Uses

For Hand Sanitizing

Warnings

For external use only.

Flammable.Keep away from fire or flame.

When using this product

Do not use in or near the eyes.In case of contact with eyes flush thoroughly with water

Use wipes only on unbroken, intact skin

lf you have sensitive skin or certain allergies,

check the list of ingredients on the label before using wipes

Do not ingest

Stop use and ask a doctor

lf skin irritation or redness develops

Directions

Wipe hands thoroughly, let skin dry and discard

Keep out of reach of children.Children under 6 years of age use

only under adult supervision

Not recommended for infants

Other information

Do not store above 105°F

May discolor some fabrics

Inactive ingredient

Water

Package Label - Principal Display Panel

78505-002-21 12 CLOTH in 1 BAG
78505-002-22 100 CLOTH in 1 BAG
78505-002-23 100 CLOTH in 1 BOTTLE
78505-002-24 120 CLOTH in 1 BOTTLE

78505-002-25 160 CLOTH in 1 BOTTLE
78505-002-26 180 CLOTH in 1 BOTTLE
78505-002-27 240 CLOTH in 1 BOTTLE
78505-002-28 300 CLOTH in 1 BOTTLE

78505-002-29 360 CLOTH in 1 BOTTLE
78505-002-30 400 CLOTH in 1 BOTTLE

78505-002-01 1 CLOTH in 1 BAG

78505-002-02 5 CLOTH in 1 BAG

78505-002-03 10 CLOTH in 1 BAG

78505-002-04 20 CLOTH in 1 BAG

78505-002-05 40 CLOTH in 1 BAG

78505-002-06 50 CLOTH in 1 BAG

78505-002-07 60 CLOTH in 1 BAG

78505-002-08 70 CLOTH in 1 BOTTLE

78505-002-09 72 CLOTH in 1 BOTTLE

78505-002-10 80 CLOTH in 1 BAG

78505-002-41 15pcs bag

78505-002-42 25pcs bag

78505-002-43 30pcs bag

78505-002-44 36pcs bag

78505-002-45 50PCS BOTTLE

78505-002-46 75PCS BOTTLE

78505-002-47 80PCS BOTTLE

78505-002-48 140PCS BOTTLE

78505-002-49 150PCS BOTTLE

78505-002-50 200PCS BOTTLE